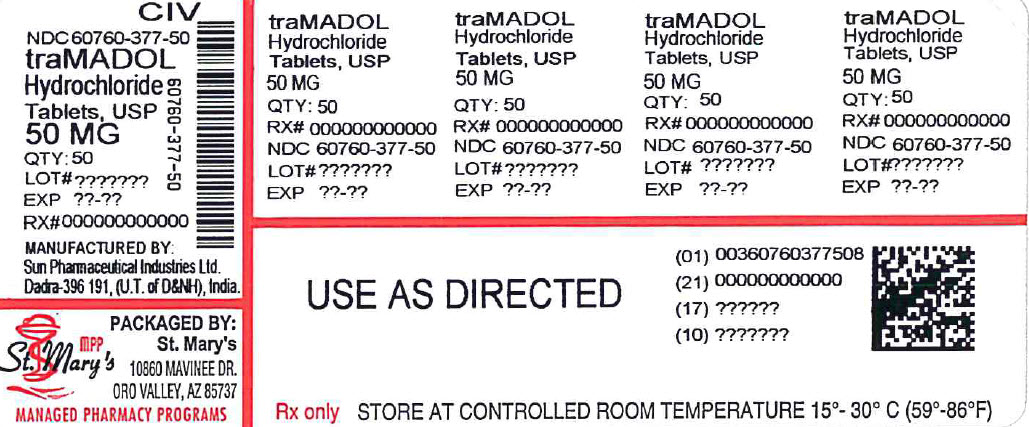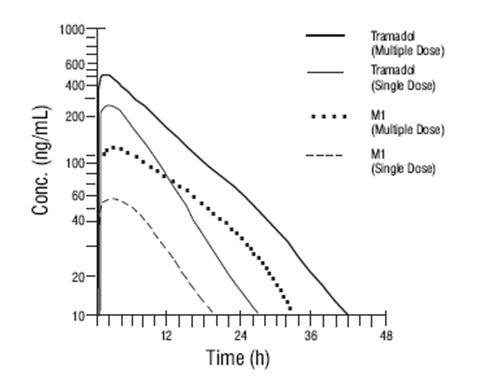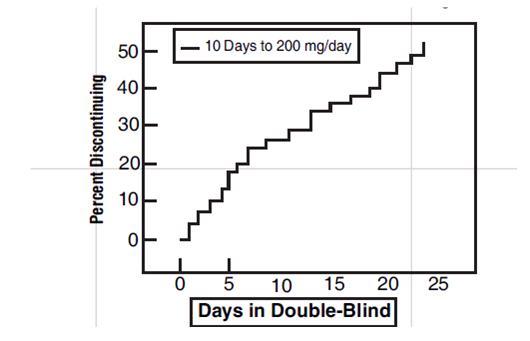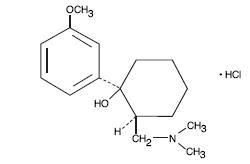 DRUG LABEL: tramadol hydrochloride
NDC: 60760-377 | Form: TABLET
Manufacturer: St. Mary's Medical Park Pharmacy
Category: prescription | Type: HUMAN PRESCRIPTION DRUG LABEL
Date: 20231208
DEA Schedule: CIV

ACTIVE INGREDIENTS: TRAMADOL HYDROCHLORIDE 50 mg/1 1
INACTIVE INGREDIENTS: STARCH, CORN; ANHYDROUS LACTOSE; MAGNESIUM STEARATE; CELLULOSE, MICROCRYSTALLINE; POLYETHYLENE GLYCOL, UNSPECIFIED; SODIUM STARCH GLYCOLATE TYPE A POTATO; TITANIUM DIOXIDE

Tramadol Hydrochloride Tablets, USP, CIV
50 mg - Rx only

DESCRIPTION

Tramadol hydrochloride tablet, USP is a centrally acting analgesic. The chemical name for tramadol hydrochloride, USP is (±) cis-2-[(dimethylamino)methyl]-1-(3-methoxyphenyl) cyclohexanol hydrochloride. Its structural formula is:

Molecular formula is C16H13NO2•HCl

The molecular weight of tramadol hydrochloride, USP is 299.8. Tramadol hydrochloride, USP is a white, bitter, crystalline and odorless powder. It is readily soluble in water and ethanol and has a pKa of 9.41. The n-octanol/water log partition coefficient (logP) is 1.35 at pH7. Tramadol hydrochloride tablets, USP for oral administration contain 50 mg of tramadol hydrochloride, USP. In addition, each tablet contains the following inactive ingredients: pregelatinized starch, lactose anhydrous, magnesium stearate, microcrystalline cellulose, polyethylene glycol, sodium starch glycolate, titanium dioxide, hypromellose and polysorbate 80.

CLINICAL PHARMACOLOGY

Pharmacodynamics

Tramadol hydrochloride is a centrally acting synthetic opioid analgesic. Although its mode of action is not completely understood, from animal tests, at least two complementary mechanisms appear applicable: binding of parent and M1 metabolite to µ-opioid receptors and weak inhibition of reuptake of norepinephrine and serotonin.

Opioid activity is due to both low affinity binding of the parent compound and higher affinity binding of the O-demethylated metabolite M1 to µ-opioid receptors. In animal models, M1 is up to 6 times more potent than tramadol in producing analgesia and 200 times more potent in µ-opioid binding. Tramadol-induced analgesia is only partially antagonized by the opiate antagonist naloxone in several animal tests. The relative contribution of both tramadol and M1 to human analgesia is dependent upon the plasma concentrations of each compound (see CLINICAL PHARMACOLOGY, Pharmacokinetics).

Tramadol has been shown to inhibit reuptake of norepinephrine and serotonin in vitro, as have some other opioid analgesics. These mechanisms may contribute independently to the overall analgesic profile of tramadol hydrochloride tablets. Analgesia in humans begins approximately within one hour after administration and reaches a peak in approximately two to three hours.

Apart from analgesia, tramadol hydrochloride tablets administration may produce a constellation of symptoms (including dizziness, somnolence, nausea, constipation, sweating and pruritus) similar to that of other opioids. In contrast to morphine, tramadol has not been shown to cause histamine release. At therapeutic doses, tramadol hydrochloride tablets have no effect on heart rate, left-ventricular function or cardiac index. Orthostatic hypotension has been observed.

Pharmacokinetics

The analgesic activity of tramadol hydrochloride tablets is due to both parent drug and the M1 metabolite (see CLINICAL PHARMACOLOGY, Pharmacodynamics). Tramadol is administered as a racemate and both the [-] and [+] forms of both tramadol and M1 are detected in the circulation. Linear pharmacokinetics have been observed following multiple doses of 50 and 100 mg to steady-state.

Absorption:

The mean absolute bioavailability of a 100 mg oral dose is approximately 75%. The mean peak plasma concentration of racemic tramadol and M1 occurs at two and three hours, respectively, after administration in healthy adults. In general, both enantiomers of tramadol and M1 follow a parallel time course in the body following single and multiple doses although small differences (~10%) exist in the absolute amount of each enantiomer present.

Steady-state plasma concentrations of both tramadol and M1 are achieved within two days with four times per day dosing. There is no evidence of self-induction (see Figure 1 and Table 1 below).

Figure 1: Mean Tramadol and M1 Plasma Concentration Profiles after a Single 100 mg Oral Dose and after Twenty-Nine 100 mg Oral Doses of Tramadol HCl given four times per day.

Table 1 Mean (%CV) Pharmacokinetic Parameters for Racemic Tramadol and M1 Metabolite
Population/ Dosage Regimena | Parent Drug/ Metabolite | Peak Conc. (ng/mL) | Time to Peak (hrs) | Clearance/Fb (mL/min/kg) | t1/2 (hrs)
Healthy Adults, 100 mg q.i.d., MD p.o. | Tramadol | 592 (30) | 2.3 (61) | 5.90 (25) | 6.7 (15)
Healthy Adults, 100 mg q.i.d., MD p.o. | M1 | 110 (29) | 2.4 (46) | c | 7.0 (14)
Healthy Adults, 100 mg SD p.o. | Tramadol | 308 (25) | 1.6 (63) | 8.50 (31) | 5.6 (20)
Healthy Adults, 100 mg SD p.o. | M1 | 55.0 (36) | 3.0 (51) | c | 6.7 (16)
Geriatric, (> 75 yrs) 50 mg SD p.o. | Tramadol | 208 (31) | 2.1 (19) | 6.89 (25) | 7.0 (23)
Geriatric, (> 75 yrs) 50 mg SD p.o. | M1 | d | d | c | d
Hepatic Impaired 50 mg SD p.o. | Tramadol | 217 (11) | 1.9 (16) | 4.23 (56) | 13.3 (11)
Hepatic Impaired 50 mg SD p.o. | M1 | 19.4 (12) | 9.8 (20) | c | 18.5 (15)
Renal Impaired CLcr 10-30 mL/min 100 mg SD i.v. | Tramadol | c | c | 4.23 (54) | 10.6 (31)
Renal Impaired CLcr 10-30 mL/min 100 mg SD i.v. | M1 | c | c | c | 11.5 (40)
Renal Impaired CLcr <5 mL/min 100 mg SD i.v. | Tramadol | c | c | 3.73 (17) | 11.0 (29)
Renal Impaired CLcr <5 mL/min 100 mg SD i.v. | M1 | c | c | c | 16.9 (18)
a SD = Single dose, MD = Multiple dose, p.o. = Oral administration, i.v. = Intravenous administration,
qid = Four times daily
b F represents the oral bioavailability of tramadol
c Not applicable
d Not measured

Food Effects:

Oral administration of tramadol hydrochloride tablets with food does not significantly affect its rate or extent of absorption, therefore, tramadol hydrochloride tablets can be administered without regard to food.

Distribution:

The volume of distribution of tramadol was 2.6 and 2.9 liters/kg in male and female subjects, respectively, following a 100 mg intravenous dose. The binding of tramadol to human plasma proteins is approximately 20% and binding also appears to be independent of concentration up to 10 µg/mL. Saturation of plasma protein binding occurs only at concentrations outside the clinically relevant range.

Metabolism:

Tramadol is extensively metabolized after oral administration by a number of pathways, including CYP2D6 and CYP3A4, as well as by conjugation of parent and metabolites. Approximately 30% of the dose is excreted in the urine as unchanged drug, whereas 60% of the dose is excreted as metabolites. The remainder is excreted either as unidentified or as unextractable metabolites. The major metabolic pathways appear to be N- and O-demethylation and glucuronidation or sulfation in the liver. One metabolite (O-desmethyltramadol, denoted M1) is pharmacologically active in animal models. Formation of M1 is dependent on CYP2D6 and as such is subject to inhibition, which may affect the therapeutic response (see PRECAUTIONS-Drug Interaction).

Approximately 7% of the population has reduced activity of the CYP2D6 isoenzyme of cytochrome P-450. These individuals are “poor metabolizers” of debrisoquine, dextromethorphan, tricyclic antidepressants, among other drugs. Based on a population PK analysis of Phase l studies in healthy subjects, concentrations of tramadol were approximately 20% higher in “poor metabolizers” versus “extensive metabolizers”, while M1 concentrations were 40% lower. Concomitant therapy with inhibitors of CYP2D6 such as fluoxetine, paroxetine, and quinidine could result in significant drug interactions. In vitro drug interaction studies in human liver microsomes indicate that inhibitors of CYP2D6 such as fluoxetine and its metabolite norfluoxetine, amitriptyline and quinidine inhibit the metabolism of tramadol to various degrees, suggesting that concomitant administration of these compounds could result in increases in tramadol concentrations and decreased concentrations of M1. The full pharmacological impact of these alterations in terms of either efficacy or safety is unknown. Concomitant use of SEROTONIN re-uptake INHIBITORS and MAO INHIBITORS may enhance the risk of adverse events, including seizure (see WARNINGS) and serotonin syndrome.

Elimination:

Tramadol is eliminated primarily through metabolism by the liver and the metabolites are eliminated primarily by the kidneys. The mean terminal plasma elimination half-lives of racemic tramadol and racemic M1 are 6.3 ± 1.4 and 7.4 ± 1.4 hours, respectively. The plasma elimination half-life of racemic tramadol increased from approximately six hours to seven hours upon multiple dosing.

Special Populations

Renal:

Impaired renal function results in a decreased rate and extent of excretion of tramadol and its active metabolite, M1. In patients with creatinine clearances of less than 30 mL/min, adjustment of the dosing regimen is recommended (see DOSAGE AND ADMINISTRATION). The total amount of tramadol and M1 removed during a 4-hour dialysis period is less than 7% of the administered dose.

Hepatic:

Metabolism of tramadol and M1 is reduced in patients with advanced cirrhosis of the liver, resulting in both a larger area under the concentration time curve for tramadol and longer tramadol and M1 elimination half-lives (13 hrs. for tramadol and 19 hrs. for M1). In cirrhotic patients, adjustment of the dosing regimen is recommended (see DOSAGE AND ADMINISTRATION).

Geriatric:

Healthy elderly subjects aged 65 to 75 years have plasma tramadol concentrations and elimination half-lives comparable to those observed in healthy subjects less than 65 years of age. In subjects over 75 years, maximum serum concentrations are elevated (208 vs. 162 ng/mL) and the elimination half-life is prolonged (7 vs. 6 hours) compared to subjects 65 to 75 years of age. Adjustment of the daily dose is recommended for patients older than 75 years (see DOSAGE AND ADMINISTRATION).

Gender:

The absolute bioavailability of tramadol was 73% in males and 79% in females. The plasma clearance was 6.4 mL/min/kg in males and 5.7 mL/min/kg in females following a 100 mg IV dose of tramadol. Following a single oral dose, and after adjusting for body weight, females had a 12% higher peak tramadol concentration and a 35% higher area under the concentration-time curve compared to males. The clinical significance of this difference is unknown.

Clinical Studies

Tramadol hydrochloride tablets have been given in single oral doses of 50, 75, and 100 mg to patients with pain following surgical procedures and pain following oral surgery (extraction of impacted molars).

In single-dose models of pain following oral surgery, pain relief was demonstrated in some patients at doses of 50 mg and 75 mg. A dose of 100 mg tramadol hydrochloride tablets tended to provide analgesia superior to codeine sulfate 60 mg, but it was not as effective as the combination of aspirin 650 mg with codeine phosphate 60 mg.

Tramadol hydrochloride tablets have been studied in three long-term controlled trials involving a total of 820 patients, with 530 patients receiving tramadol hydrochloride tablets. Patients with a variety of chronic painful conditions were studied in double-blind trials of one to three months duration. Average daily doses of approximately 250 mg of tramadol hydrochloride tablets in divided doses were generally comparable to five doses of acetaminophen 300 mg with codeine phosphate 30 mg (TYLENOL® with Codeine #3) daily, five doses of aspirin 325 mg with codeine phosphate 30 mg daily, or two to three doses of acetaminophen 500 mg with oxycodone hydrochloride 5 mg (TYLOX®) daily. [TYLENOL® is the registered trademark of McNeil Consumer Healthcare and TYLOX® is the registered trademark of RW Johnson].

Titration Trials

In a randomized, blinded clinical study with 129 to 132 patients per group, a 10-day titration to a daily tramadol hydrochloride dose of 200 mg (50 mg four times per day), attained in 50 mg increments every 3 days, was found to result in fewer discontinuations due to dizziness or vertigo than titration over only 4 days or no titration.

Figure 2: Protocol CAPSS-047
Time to Discontinuation Due to Nausea/Vomiting

INDICATIONS AND USAGE

Tramadol hydrochloride tablets, USP are indicated for the management of moderate to moderately severe pain in adults.

CONTRAINDICATIONS

Tramadol hydrochloride tablets should not be administered to patients who have previously demonstrated hypersensitivity to tramadol, any other component of this product or opioids. Tramadol hydrochloride is contraindicated in any situation where opioids are contraindicated, including acute intoxication with any of the following: alcohol, hypnotics, narcotics, centrally acting analgesics, opioids or psychotropic drugs. Tramadol may worsen central nervous system and respiratory depression in these patients.

WARNINGS

Seizure Risk

Seizures have been reported in patients receiving tramadol hydrochloride tablets within the recommended dosage range. Spontaneous post-marketing reports indicate that seizure risk is increased with doses of tramadol hydrochloride tablets above the recommended range. Concomitant use of tramadol hydrochloride tablets increases the seizure risk in patients taking:

- Selective serotonin reuptake inhibitors (SSRI antidepressants or anorectics),
- Tricyclic antidepressants (TCAs), and other tricyclic compounds (e.g., cyclobenzaprine, promethazine, etc.), or
- Other opioids.

Administration of tramadol hydrochloride tablets may enhance the seizure risk in patients taking:

- MAO inhibitors (see also WARNINGS - Use with MAO inhibitors, and Serotonin Re-Uptake Inhibitors)
- Neuroleptics, or
- Other drugs that reduce the seizure threshold.

Risk of convulsions may also increase in patients with epilepsy, those with a history of seizures, or in patients with a recognized risk for seizure (such as head trauma, metabolic disorders, alcohol and drug withdrawal, CNS infections). In tramadol hydrochloride tablets overdose, naloxone administration may increase the risk of seizure.

Suicide Risk

Do not prescribe tramadol hydrochloride tablets for patients who are suicidal or addiction-prone.

Prescribe tramadol hydrochloride tablets with caution for patients who are taking tranquilizers or antidepressant drug and patients who use alcohol in excess and who suffer from emotional disturbance or depression.

The judicious prescribing of tramadol is essential to the safe use of this drug. With patients who are depressed or suicidal, consideration should be given to the use of non-narcotic analgesics.

Tramadol-related deaths have occurred in patients with previous histories of emotional disturbances or suicidal ideation or attempts as well as histories of misuse of tranquilizers, alcohol, and other CNS-active drugs (see WARNINGS, Risk of Overdosage).

Serotonin Syndrome Risk

The development of a potentially life-threatening serotonin syndrome may occur with the use of tramadol products, including tramadol hydrochloride tablets, particularly with concomitant use of serotonergic drugs such as SSRIs, SNRIs, TCAs, MAOIs, and triptans, with drugs which impair metabolism of serotonin (including MAOIs), and with drugs which impair metabolism of tramadol (CYP2D6 and CYP3A4 inhibitors). This may occur within the recommended dose (see CLINICAL PHARMACOLOGY, Pharmacokinetics).

Serotonin syndrome may include mental-status changes (e.g., agitation, hallucinations, coma), autonomic instability (e.g., tachycardia, labile blood pressure, hyperthermia), neuromuscular aberrations (e.g., hyperreflexia, incoordination) and/or gastrointestinal symptoms (e.g., nausea, vomiting, diarrhea).

Anaphylactoid Reactions

Serious and rarely fatal anaphylactoid reactions have been reported in patients receiving therapy with tramadol hydrochloride tablets. When these events do occur it is often following the first dose. Other reported allergic reactions include pruritus, hives, bronchospasm, angioedema, toxic epidermal necrolysis and Stevens Johnson syndrome. Patients with a history of anaphylactoid reactions to codeine and other opioids may be at increased risk and therefore should not receive tramadol hydrochloride tablets (see CONTRAINDICATIONS).

Respiratory Depression

Administer tramadol hydrochloride tablets cautiously in patients at risk for respiratory depression. In these patients alternative non-opioid analgesics should be considered. When large doses of tramadol hydrochloride tablets are administered with anesthetic medications or alcohol, respiratory depression may result. Respiratory depression should be treated as an overdose. If naloxone is to be administered, use cautiously because it may precipitate seizures (see WARNINGS, Seizure Risk and OVERDOSAGE).

Interaction with Central Nervous System (CNS) Depressants

Tramadol should be used with caution and in reduced dosages when administered to patients receiving CNS depressants such as alcohol, opioids, anesthetic agents, narcotics, phenothiazines, tranquilizers or sedative hypnotics. Tramadol increases the risk of CNS and respiratory depression in these patients.

Interactions with Alcohol and Drugs of Abuse

Tramadol may be expected to have additive effects when used in conjunction with alcohol, other opioids, or illicit drugs that cause central nervous system depression.

Increased Intracranial Pressure or Head Trauma

Tramadol hydrochloride tablets should be used with caution in patients with increased intracranial pressure or head injury. The respiratory depressant effects of opioids include carbon dioxide retention and secondary elevation of cerebrospinal fluid pressure, and may be markedly exaggerated in these patients. Additionally, pupillary changes (miosis) from tramadol may obscure the existence, extent, or course of intracranial pathology. Clinicians should also maintain a high index of suspicion for adverse drug reaction when evaluating altered mental status in these patients if they are receiving tramadol hydrochloride tablets. (See WARNINGS, Respiratory Depression)

Use in Ambulatory Patients

Tramadol may impair the mental and or physical abilities required for the performance of potentially hazardous tasks such as driving a car or operating machinery. The patients using this drug should be cautioned accordingly.

Use with MAO Inhibitors and serotonin re-uptake inhibitors

Use tramadol hydrochloride tablets with great caution in patients taking monoamine oxidase inhibitors. Animal studies have shown increased deaths with combined administration. Concomitant use of tramadol hydrochloride tablets with MAO inhibitors or SSRI's increases the risk of adverse events, including seizure and serotonin syndrome.

Misuse, Abuse and Diversion

Tramadol has mu-opioid agonist activity. Tramadol hydrochloride tablets can be sought by drug abusers and people with addiction disorders and may be subject to criminal diversion. The possibility of illegal or illicit use should be considered when prescribing or dispensing Tramadol hydrochloride tablets in situations where the physician or pharmacist is concerned about an increased risk of misuse, abuse, or diversion. Misuse or abuse poses a significant risk to the abuser that could result in overdose and death (see DRUG ABUSE AND DEPENDENCE and OVERDOSAGE).

Concerns about abuse, addiction, and diversion should not prevent the proper management of pain. The development of addiction to opioid analgesics in properly managed patients with pain has been reported to be rare. However, data are not available to establish the true incidence of addiction in chronic pain patients.

Risk of Overdosage

Patients taking tramadol should be warned not to exceed the dose recommended by their physician. Tramadol products in excessive doses, either alone or in combination with other CNS depressants, including alcohol, are a cause of drug-related deaths. Patients should be cautioned about the concomitant use of tramadol products and alcohol because of potentially serious CNS additive effects of these agents. Because of its added depressant effects, tramadol should be prescribed with caution for those patients whose medical condition requires the concomitant administration of sedatives, tranquilizers, muscle relaxants, antidepressants, or other CNS depressant drugs. Patients should be advised of the additive depressant effects of these combinations.

Serious potential consequences of overdosage with tramadol hydrochloride tablets are central nervous system depression, respiratory depression and death. Some deaths have occurred as a consequence of the accidental ingestion of excessive quantities of tramadol alone or in combination with other drugs. In treating an overdose, primary attention should be given to maintaining adequate ventilation along with general supportive treatment (see OVERDOSAGE).

Withdrawal

Withdrawal symptoms may occur if tramadol hydrochloride tablets are discontinued abruptly. (See also DRUG ABUSE and DEPENDENCE) Reported symptoms have included anxiety, sweating, insomnia, rigors, pain, nausea, tremors, diarrhea, upper respiratory symptoms, piloerection, and rarely hallucinations. Other symptoms that have been reported less frequently with tramadol hydrochloride tablets discontinuation include panic attacks, severe anxiety, and paresthesias. Clinical experience suggests that withdrawal symptoms may be avoided by tapering tramadol hydrochloride tablets at the time of discontinuation.

PRECAUTIONS

Acute Abdominal Conditions

The administration of tramadol hydrochloride tablets may complicate the clinical assessment of patients with acute abdominal conditions.

Use in Renal and Hepatic Disease

Impaired renal function results in a decreased rate and extent of excretion of tramadol and its active metabolite, M1. In patients with creatinine clearances of less than 30 mL/min, dosing reduction is recommended (see DOSAGE AND ADMINISTRATION).

Metabolism of tramadol and M1 is reduced in patients with advanced cirrhosis of the liver. In cirrhotic patients, dosing reduction is recommended (see DOSAGE AND ADMINISTRATION).

With the prolonged half-life in these conditions, achievement of steady-state is delayed, so that it may take several days for elevated plasma concentrations to develop.

Information for Patients

- Patients should be informed that tramadol hydrochloride tablets may cause seizures and/or serotonin syndrome with concomitant use of serotonergic agents (including SSRIs, SNRIs, and triptans) or drugs that significantly reduce the metabolic clearance of tramadol.
- Tramadol hydrochloride tablets may impair mental or physical abilities required for the performance of potentially hazardous tasks such as driving a car or operating machinery.
- Tramadol hydrochloride tablets should not be taken with alcohol containing beverages.
- Tramadol hydrochloride tablets should be used with caution when taking medications such as tranquilizers, hypnotics or other opiate containing analgesics.
- The patient should be instructed to inform the physician if they are pregnant, think they might become pregnant, or are trying to become pregnant (see PRECAUTIONS: Labor and Delivery).
- The patient should understand the single-dose and 24-hour dose limit and the time interval between doses, since exceeding these recommendations can result in respiratory depression, seizures and death.

Drug Interactions

CYP2D6 and CYP3A4 Inhibitors

Concomitant administration of CYP2D6 and/or CYP3A4 inhibitors (see CLINICAL PHARMACOLOGY, Pharmacokinetics), such as quinidine, fluoxetine, paroxetine and amitriptyline (CYP2D6 inhibitors), and ketoconazole and erythromycin (CYP3A4 inhibitors), may reduce metabolic clearance of tramadol increasing the risk for serious adverse events including seizures and serotonin syndrome.

Serotonergic Drugs

There have been postmarketing reports of serotonin syndrome with use of tramadol and SSRIs/SNRIs or MAOIs and α2-adrenergic blockers. Caution is advised when tramadol hydrochloride tablet is coadministered with other drugs that may affect the serotonergic neurotransmitter systems, such as SSRIs, MAOIs, triptans, linezolid (an antibiotic which is a reversible non-selective MAOI), lithium, or St. John's Wort. If concomitant treatment of tramadol hydrochloride tablet with a drug affecting the serotonergic neurotransmitter system is clinically warranted, careful observation of the patient is advised, particularly during treatment initiation and dose increases (see WARNINGS, Serotonin Syndrome).

Triptans

Based on the mechanism of action of tramadol and the potential for serotonin syndrome, caution is advised when tramadol hydrochloride tablet is coadministered with a triptan. If concomitant treatment of tramadol hydrochloride tablet with a triptan is clinically warranted, careful observation of the patient is advised, particularly during treatment initiation and dose increases (see WARNINGS, Serotonin Syndrome).

Use with Carbamazepine

Patients taking carbamazepine may have a significantly reduced analgesic effect of tramadol hydrochloride tablets. Because carbamazepine increases tramadol metabolism and because of the seizure risk associated with tramadol, concomitant administration of tramadol hydrochloride tablets and carbamazepine is not recommended.

Use with Quinidine

Tramadol is metabolized to M1 by CYP2D6. Quinidine is a selective inhibitor of that isoenzyme, so that concomitant administration of quinidine and tramadol hydrochloride tablets results in increased concentrations of tramadol and reduced concentrations of M1. The clinical consequences of these findings are unknown. In vitro drug interaction studies in human liver microsomes indicate that tramadol has no effect on quinidine metabolism.

Potential for Other Drugs to Affect Tramadol

In vitro drug interaction studies in human liver microsomes indicate that concomitant administration with inhibitors of CYP2D6 such as fluoxetine, paroxetine, and amitriptyline could result in some inhibition of the metabolism of tramadol. Administration of CYP3A4 inhibitors, such as ketoconazole and erythromycin, or inducers, such as rifampin and St. John's Wort, with tramadol hydrochloride tablet may affect the metabolism of tramadol leading to altered tramadol exposure.

Potential for Tramadol to Affect Other Drugs

In vitro studies indicate that tramadol is unlikely to inhibit the CYP3A4-mediated metabolism of other drugs when tramadol is administered concomitantly at therapeutic doses. Tramadol does not appear to induce its own metabolism in humans, since observed maximal plasma concentrations after multiple oral doses are higher than expected based on single-dose data. Tramadol is a mild inducer of selected drug metabolism pathways measured in animals.

Use with Cimetidine

Concomitant administration of tramadol hydrochloride tablets with cimetidine does not result in clinically significant changes in tramadol pharmacokinetics. Therefore, no alteration of the tramadol hydrochloride tablets dosage regimen is recommended.

Use with Digoxin and Warfarin

Post-marketing surveillance has revealed rare reports of digoxin toxicity and alteration of warfarin effect, including elevation of prothrombin times.

Carcinogenesis, Mutagenesis, Impairment of Fertility

A slight, but statistically significant, increase in two common murine tumors, pulmonary and hepatic, was observed in a mouse carcinogenicity study, particularly in aged mice. Mice were dosed orally up to 30 mg/kg (90 mg/m^2 or 0.36 times the maximum daily human dosage of 246 mg/ m^2) for approximately two years, although the study was not done with the Maximum Tolerated Dose. This finding is not believed to suggest risk in humans. No such finding occurred in a rat carcinogenicity study (dosing orally up to 30 mg/kg, 180 mg/ m^2, or 0.73 times the maximum daily human dosage).

Tramadol was not mutagenic in the following assays: Ames Salmonella microsomal activation test, CHO/HPRT mammalian cell assay, mouse lymphoma assay (in the absence of metabolic activation), dominant lethal mutation tests in mice, chromosome aberration test in Chinese hamsters, and bone marrow micronucleus tests in mice and Chinese hamsters. Weakly mutagenic results occurred in the presence of metabolic activation in the mouse lymphoma assay and micronucleus test in rats. Overall, the weight of evidence from these tests indicates that tramadol does not pose a genotoxic risk to humans.

No effects on fertility were observed for tramadol at oral dose levels up to 50 mg/kg (300 mg/ m^2) in male rats and 75 mg/kg (450 mg/ m^2) in female rats. These dosages are 1.2 and 1.8 times the maximum daily human dosage of 246 mg/ m^2, respectively.

Pregnancy

Teratogenic Effects: Pregnancy Category C

Tramadol has been shown to be embryotoxic and fetotoxic in mice, (120 mg/kg or 360 mg/ m^2) rats (≥25 mg/kg or 150 mg/ m^2) and rabbits (≥75 mg/kg or 900 mg/ m^2) at maternally toxic doses, but was not teratogenic at these dose levels. These dosages on a mg/ m^2 basis are 1.4, ≥0.6, and ≥3.6 times the maximum daily human dosage (246 mg/ m^2) for mouse, rat and rabbit, respectively.

No drug-related teratogenic effects were observed in progeny of mice, (up to 140 mg/kg or 420 mg/ m^2), rats (up to 80 mg/kg or 480 mg/ m^2) or rabbits (up to 300 mg/kg or 3600 mg/ m^2) treated with tramadol by various routes. Embryo and fetal toxicity consisted primarily of decreased fetal weights, skeletal ossification and increased supernumerary ribs at maternally toxic dose levels. Transient delays in developmental or behavioral parameters were also seen in pups from rat dams allowed to deliver. Embryo and fetal lethality were reported only in one rabbit study at 300 mg/kg (3600 mg/ m^2), a dose that would cause extreme maternal toxicity in the rabbit. The dosages listed for mouse, rat and rabbit are 1.7, 1.9 and 14.6 times the maximum daily human dosage (246 mg/ m^2), respectively.

Non-teratogenic Effects

Tramadol was evaluated in peri- and post-natal studies in rats. Progeny of dams receiving oral (gavage) dose levels of 50 mg/kg (300 mg/ m^2 or 1.2 times the maximum daily human tramadol dosage) or greater had decreased weights, and pup survival was decreased early in lactation at 80 mg/kg (480 mg/ m^2 or 1.9 and higher the maximum daily human dose).

There are no adequate and well-controlled studies in pregnant women. Tramadol hydrochloride tablets should be used during pregnancy only if the potential benefit justifies the potential risk to the fetus. Neonatal seizures, neonatal withdrawal syndrome, fetal death and still birth have been reported during post-marketing.

Labor and Delivery

Tramadol hydrochloride tablets should not be used in pregnant women prior to or during labor unless the potential benefits outweigh the risks. Safe use in pregnancy has not been established. Chronic use during pregnancy may lead to physical dependence and post-partum withdrawal symptoms in the newborn. (See DRUG ABUSE and DEPENDENCE). Tramadol has been shown to cross the placenta. The mean ratio of serum tramadol in the umbilical veins compared to maternal veins was 0.83 for 40 women given tramadol during labor.

The effect of tramadol hydrochloride tablets, if any, on the later growth, development, and functional maturation of the child is unknown.

Nursing Mothers

Tramadol hydrochloride tablets are not recommended for obstetrical preoperative medication or for post delivery analgesia in nursing mothers because its safety in infants and newborns has not been studied. Following a single IV 100 mg dose of tramadol, the cumulative excretion in breast milk within 16 hours post-dose was 100 µg of tramadol (0.1% of the maternal dose) and 27 µg of M1.

Pediatric Use

The safety and efficacy of tramadol hydrochloride tablets in patients under 16 years of age have not been established. The use of tramadol in the pediatric population is not recommended.

Geriatric Use

In general, dose selection for an elderly patient should be cautious, usually starting at the low end of the dosing range, reflecting the greater frequency of decreased hepatic, renal or cardiac function and of concomitant disease or other drug therapy. In patients over 75 years of age, daily doses in excess of 300 mg are not recommended. (see CLINICAL PHARMACOLOGY and DOSAGE AND ADMINISTRATION).

A total of 455 elderly (65 years of age or older) subjects were exposed to tramadol hydrochloride tablets in controlled clinical trials. Of those, 145 subjects were 75 years of age and older.

In studies including geriatric patients, treatment-limiting adverse events were higher in subjects over 75 years of age compared to those under 65 years of age. Specifically, 30% of those over 75 years of age had gastrointestinal treatment-limiting adverse events compared to 17% of those under 65 years of age. Constipation resulted in discontinuation of treatment in 10% of those over 75.

ADVERSE REACTIONS

Tramadol hydrochloride tablets were administered to 550 patients during the double-blind or open-label extension periods in U.S. studies of chronic nonmalignant pain. Of these patients, 375 were 65 years old or older. Table 2 reports the cumulative incidence rate of adverse reactions by 7, 30, and 90 days for the most frequent reactions (5% or more by 7 days). The most frequently reported events were in the central nervous system and gastrointestinal system. Although the reactions listed in the table are felt to be probably related to tramadol hydrochloride tablets administration, the reported rates also include some events that may have been due to underlying disease or concomitant medication. The overall incidence rates of adverse experiences in these trials were similar for tramadol hydrochloride tablets and the active control groups, TYLENOL® with codeine #3 (acetaminophen 300 mg with codeine phosphate 30 mg), and aspirin 325 mg with codeine phosphate 30 mg however the rates of withdrawals due to adverse events appeared to be higher in the tramadol hydrochloride groups. [TYLENOL® is the registered trademark of McNeil Consumer Healthcare and TYLOX® is the registered trademark of RW Johnson].

Table 2 Cumulative Incidence of Adverse Reactions for Tramadol Hydrochloride Tablets in Chronic Trials of Nonmalignant Pain (N=427)
 | Up to 7 Days | Up to 30 Days | Up to 90 Days
Dizziness/Vertigo | 26% | 31% | 33%
Nausea | 24% | 34% | 40%
Constipation | 24% | 38% | 46%
Headache | 18% | 26% | 32%
Somnolence | 16% | 23% | 25%
Vomiting | 9% | 13% | 17%
Pruritus | 8% | 10% | 11%
“CNS Stimulation” ^1 | 7% | 11% | 14%
Asthenia | 6% | 11% | 12%
Sweating | 6% | 7% | 9%
Dyspepsia | 5% | 9% | 13%
Dry Mouth | 5% | 9% | 10%
Diarrhea | 5% | 6% | 10%
1 “CNS Stimulation” is a composite of nervousness, anxiety, agitation, tremor, spasticity, euphoria, emotional
lability and hallucinations.

Incidence 1% to less than 5%, possibly causally related: the following lists adverse reactions that occurred with an incidence of 1% to less than 5% in clinical trials, and for which the possibility of a causal relationship with tramadol hydrochloride tablets exists.

Body as a Whole: Malaise.

Cardiovascular: Vasodilation.

Central Nervous System: Anxiety, Confusion, Coordination disturbance, Euphoria, Miosis, Nervousness, Sleep disorder.

Gastrointestinal: Abdominal pain, Anorexia, Flatulence.

Musculoskeletal: Hypertonia.

Skin: Rash.

Special Senses: Visual disturbance.

Urogenital: Menopausal symptoms, Urinary frequency, Urinary retention.

Incidence less than 1%, possibly causally related: the following lists adverse reactions that occurred with an incidence of less than 1% in clinical trials and/or reported in post-marketing experience.

Body as a Whole: Accidental injury, Allergic reaction, Anaphylaxis, Death, Suicidal tendency, Weight loss, Serotonin syndrome (mental status change, hyperreflexia, fever, shivering, tremor, agitation, diaphoresis, seizures and coma).

Cardiovascular: Orthostatic hypotension, Syncope, Tachycardia.

Central Nervous System: Abnormal gait, Amnesia, Cognitive dysfunction, Depression, Difficulty in concentration, Hallucinations, Paresthesia, Seizure (see WARNINGS), Tremor.

Respiratory: Dyspnea.

Skin: Stevens-Johnson syndrome/Toxic epidermal necrolysis, Urticaria, Vesicles.

Special Senses: Dysgeusia.

Urogenital: Dysuria, Menstrual disorder.

Other adverse experiences, causal relationship unknown: A variety of other adverse events were reported infrequently in patients taking tramadol hydrochloride tablets during clinical trials and/or reported in post-marketing experience. A causal relationship between tramadol hydrochloride tablets and these events has not been determined. However, the most significant events are listed below as alerting information to the physician.

Cardiovascular: Abnormal ECG, Hypertension, Hypotension, Myocardial ischemia, Palpitations, Pulmonary edema, Pulmonary embolism.

Central Nervous System: Migraine, Speech disorders.

Gastrointestinal: Gastrointestinal bleeding, Hepatitis, Stomatitis, Liver failure.

Laboratory Abnormalities: Creatinine increase, Elevated liver enzymes, Hemoglobin decrease, Proteinuria.

Sensory: Cataracts, Deafness, Tinnitus.

DRUG ABUSE AND DEPENDENCE

Controlled Substance Class

Tramadol hydrochloride is a Schedule IV controlled substance.

Abuse

Tramadol has mu-opioid agonist activity. Tramadol Hydrochloride Tablet can be abused and may be subject to criminal diversion.

Addiction is a primary, chronic, neurobiologic disease, with genetic, psychosocial, and environmental factors influencing its development and manifestations. Drug addiction is characterized by behaviors that include one or more of the following: impaired control over drug use, compulsive use, use for non-medical purposes, and continued use despite harm or risk of harm, and craving. Drug addiction is a treatable disease, utilizing a multidisciplinary approach, but relapse is common.

"Drug-seeking" behavior is very common in addicts and drug abusers. Drug-seeking tactics include emergency calls or visits near the end of office hours, refusal to undergo appropriate examination, testing or referral, repeated "loss" of prescriptions, tampering with prescriptions and reluctance to provide prior medical records or contact information for other treating physician(s). "Doctor shopping" to obtain additional prescriptions is common among drug abusers and people suffering from untreated addiction.

Abuse and addiction are separate and distinct from physical dependence and tolerance. Physicians should be aware that addiction may not be accompanied by concurrent tolerance and symptoms of physical dependence in all addicts. In addition, abuse of tramadol hydrochloride tablet can occur in the absence of true addiction and is characterized by misuse for non-medical purposes, often in combination with other psychoactive substances. Concerns about abuse and addiction should not prevent the proper management of pain. However all patients treated with opioids require careful monitoring for signs of abuse and addiction, because use of opioid analgesic products carries the risk of addiction even under appropriate medical use.

Proper assessment of the patient and periodic re-evaluation of therapy are appropriate measures that help to limit the potential abuse of this product.

Tramadol hydrochloride tablet is intended for oral use only.

Dependence

Tolerance is the need for increasing doses of drugs to maintain a defined effect such as analgesia (in the absence of disease progression or other external factors). Physical dependence is manifested by withdrawal symptoms after abrupt discontinuation of a drug or upon administration of an antagonist (see also WARNINGS, Withdrawal).

The opioid abstinence or withdrawal syndrome is characterized by some or all of the following: restlessness, lacrimation, rhinorrhea, yawning, perspiration, chills, myalgia, and mydriasis. Other symptoms also may develop, including irritability, anxiety, backache, joint pain, weakness, abdominal cramps, insomnia, nausea, anorexia, vomiting, diarrhea, or increased blood pressure, respiratory rate, or heart rate.

Generally, tolerance and/or withdrawal are more likely to occur the longer a patient is on continuous therapy with tramadol hydrochloride tablet.

OVERDOSAGE

Acute overdosage with tramadol can be manifested by respiratory depression, somnolence progressing to stupor or coma, skeletal muscle flaccidity, cold and clammy skin, constricted pupils, seizures, bradycardia, hypotension, cardiac arrest, and death. Deaths due to overdose have been reported with abuse and misuse of tramadol (see WARNINGS, Misuse, Abuse, and Diversion). Review of case reports has indicated that the risk of fatal overdose is further increased when tramadol is abused concurrently with alcohol or other CNS depressants, including other opioids.

In the treatment of tramadol overdosage, primary attention should be given to the reestablishment of a patent airway and institution of assisted or controlled ventilation. Supportive measures (including oxygen and vasopressors) should be employed in the management of circulatory shock and pulmonary edema accompanying overdose as indicated. Cardiac arrest or arrhythmias may require cardiac massage or defibrillation.

While naloxone will reverse some, but not all, symptoms caused by overdosage with tramadol, the risk of seizures is also increased with naloxone administration. In animals convulsions following the administration of toxic doses of tramadol hydrochloride tablet could be suppressed with barbiturates or benzodiazepines but were increased with naloxone. Naloxone administration did not change the lethality of an overdose in mice. Hemodialysis is not expected to be helpful in an overdose because it removes less than 7% of the administered dose in a 4-hour dialysis period.

DOSAGE AND ADMINISTRATION

Adults (17 years of age and over)

For patients with moderate to moderately severe chronic pain not requiring rapid onset of analgesic effect, the tolerability of tramadol hydrochloride tablets can be improved by initiating therapy with the following titration regimen: The total daily dose may be increased by 50 mg as tolerated every 3 days to reach 200 mg/day (50 mg q.i.d.). After titration, tramadol hydrochloride tablets 50 mg to 100 mg can be administered as needed for pain relief every four to six hours, not to exceed 400 mg per day.

For the subset of patients for whom rapid onset of analgesic effect is required and for whom the benefits outweigh the risk of discontinuation due to adverse events associated with higher initial doses, tramadol hydrochloride tablets 50 mg to 100 mg can be administered as needed for pain relief every four to six hours, not to exceed 400 mg per day.

Individualization of Dose

Good pain management practice dictates that the dose be individualized according to patient need using the lowest beneficial dose. Studies with tramadol in adults have shown that starting at the lowest possible dose and titrating upward will result in fewer discontinuations and increased tolerability.

- In all patients with creatinine clearance less than 30 mL/min, it is recommended that the dosing interval of tramadol hydrochloride tablets be increased to 12 hours, with a maximum daily dose of 200 mg. Since only 7% of an administered dose is removed by hemodialysis, dialysis patients can receive their regular dose on the day of dialysis.
- The recommended dose for adult patients with cirrhosis is 50 mg every 12 hours.
- In general, dose selection for an elderly patient over 65 years old should be cautious, usually starting at the low end of the dosing range, reflecting the greater frequency of decreased hepatic, renal or cardiac function and of concomitant disease or other drug therapy. For elderly patients over 75 years old, total dose should not exceed 300 mg/day.

HOW SUPPLIED

Tramadol hydrochloride tablet, USP 50 mg are available as white capsule shaped film coated tablets, debossed with “377” on one side and plain on the other side.

NDCs

60760-377-09 BOTTLES OF 9

60760-377-20 BOTTLES OF 20

60760-377-30 BOTTLES OF 30

60760-377-50 BOTTLES OF 50

60760-377-60 BOTTLES OF 60

60760-377-90 BOTTLES OF 90

60760-377-98 BOTTLES OF 180 - INACTIVE

Dispense in tight container.

Store at 25°C (77°F); excursions permitted to 15 - 30°C (59 -86°F).